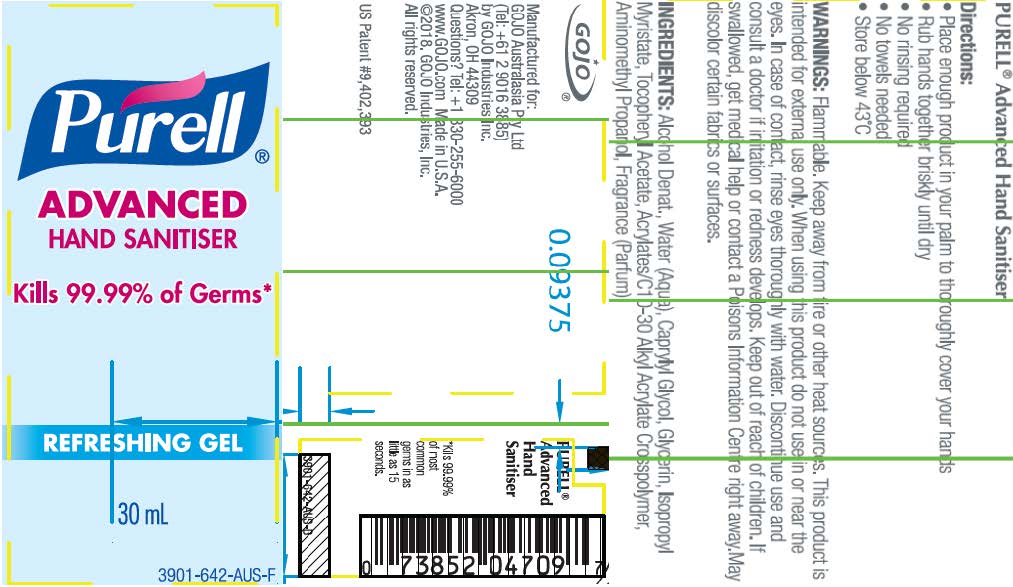 DRUG LABEL: PURELL Advanced Hand Sanitiser Gel
NDC: 21749-671 | Form: GEL
Manufacturer: GOJO Industries, Inc.
Category: otc | Type: HUMAN OTC DRUG LABEL
Date: 20260209

ACTIVE INGREDIENTS: ALCOHOL 0.7 mL/1 mL
INACTIVE INGREDIENTS: ACRYLATES/C10-30 ALKYL ACRYLATE CROSSPOLYMER (60000 MPA.S); WATER; ISOPROPYL ALCOHOL; CAPRYLYL GLYCOL; GLYCERIN; ISOPROPYL MYRISTATE; .ALPHA.-TOCOPHEROL ACETATE, D-; AMINOMETHYLPROPANOL

PURELL Advanced Instant Hand Sanitiser Gel